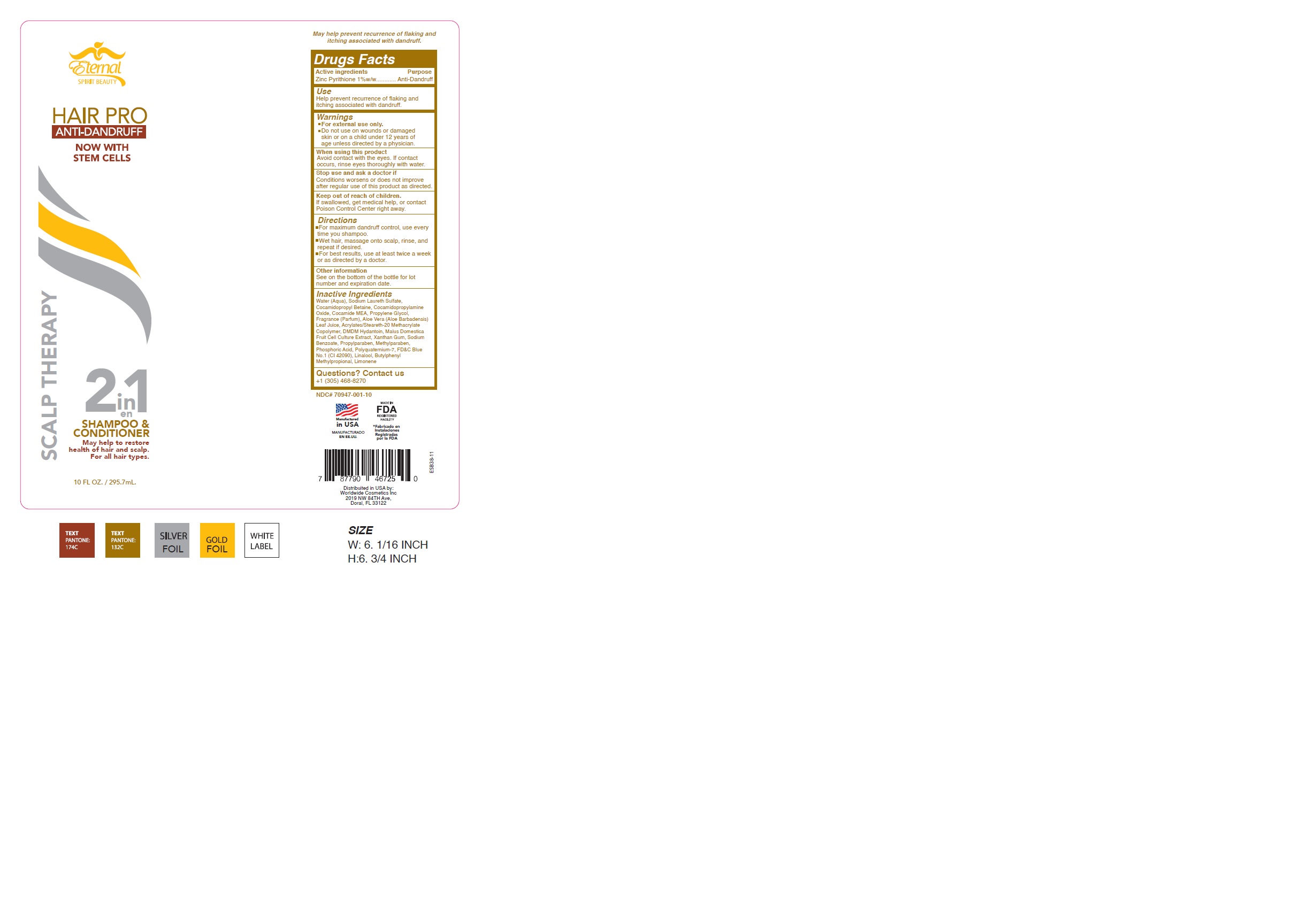 DRUG LABEL: ETERNAL SPIRIT BEAUTY HAIR PRO ANTI-DANDRUFF
NDC: 70947-001 | Form: SHAMPOO
Manufacturer: Worldwide Cosmetics, Inc
Category: otc | Type: HUMAN OTC DRUG LABEL
Date: 20241112

ACTIVE INGREDIENTS: PYRITHIONE ZINC 1 g/100 mL
INACTIVE INGREDIENTS: APPLE; XANTHAN GUM; SODIUM BENZOATE; PROPYLENE GLYCOL; SODIUM LAURETH SULFATE; COCAMIDOPROPYL BETAINE; COCAMIDOPROPYLAMINE OXIDE; ALOE VERA LEAF; PROPYLPARABEN; METHYLPARABEN; LINALOOL, (+/-)-; BUTYLPHENYL METHYLPROPIONAL; LIMONENE, (+/-)-; WATER; POLYQUATERNIUM-7 (70/30 ACRYLAMIDE/DADMAC; 900 KD); FD&C BLUE NO. 1; COCO MONOETHANOLAMIDE; ETHYL ACRYLATE/METHACRYLIC ACID/STEARETH-20 METHACRYLATE COPOLYMER; DMDM HYDANTOIN; PHOSPHORIC ACID

70947-001-10

ACTIVE INGREDIENT

Zinc Pyrithione 1%

PURPOSE

Anti-Dandruff

Use

Helps prevent recurrence of flaking and itching associated with dandruff

WARNINGS

For external use only.

Do not use on wounds or damaged skin or on a child under 12 years of age unless directed by a physician.

WHEN USING

Avoid contact with the eyes. If contact occurs, rinse eyes thoroughly with water

STOP USE

Conditions worsens or does not improve after regular use of this product as directed

KEEP OUT OF REACH OF CHILDREN

If swallowed, get medical help, or contact Poison Control Center right away

Directions

For maximum dandruff control, use every time you shampoo
Wet hair, massage onto scalp, rinse, and repeat if desired

For best results, use at least twice a week or as directed by a doctor

OTHER INFORMATION

See on the bottom of the bottle for lot number and expiration date.

INACTIVE INGREDIENT

Water (Aqua), Sodium Laureth Sulfate, Cocamidopropyl Betaine, Cocamidopropylamine Oxide, Cocamide MEA, Propylene Glycol, Fragrance (Parfum), Aloe Vera (Aloe Barbadensis) Leaf Juice, Acrylates/Steareth-20 Methacrylate Copolymer, DMDM Hydantoin, Malus Domestica Fruit Cell Culture Extract, Xanthan Gum, Sodium Benzoate, Propylparaben, Methylparaben, Phosphoric Acid, Polyquaternium-7, FD&C Blue No.1 (CI 42090), Linalool, Butylphenyl Methylpropional, Limonene

Questions or comments?

Contact us +1-305-468-8270